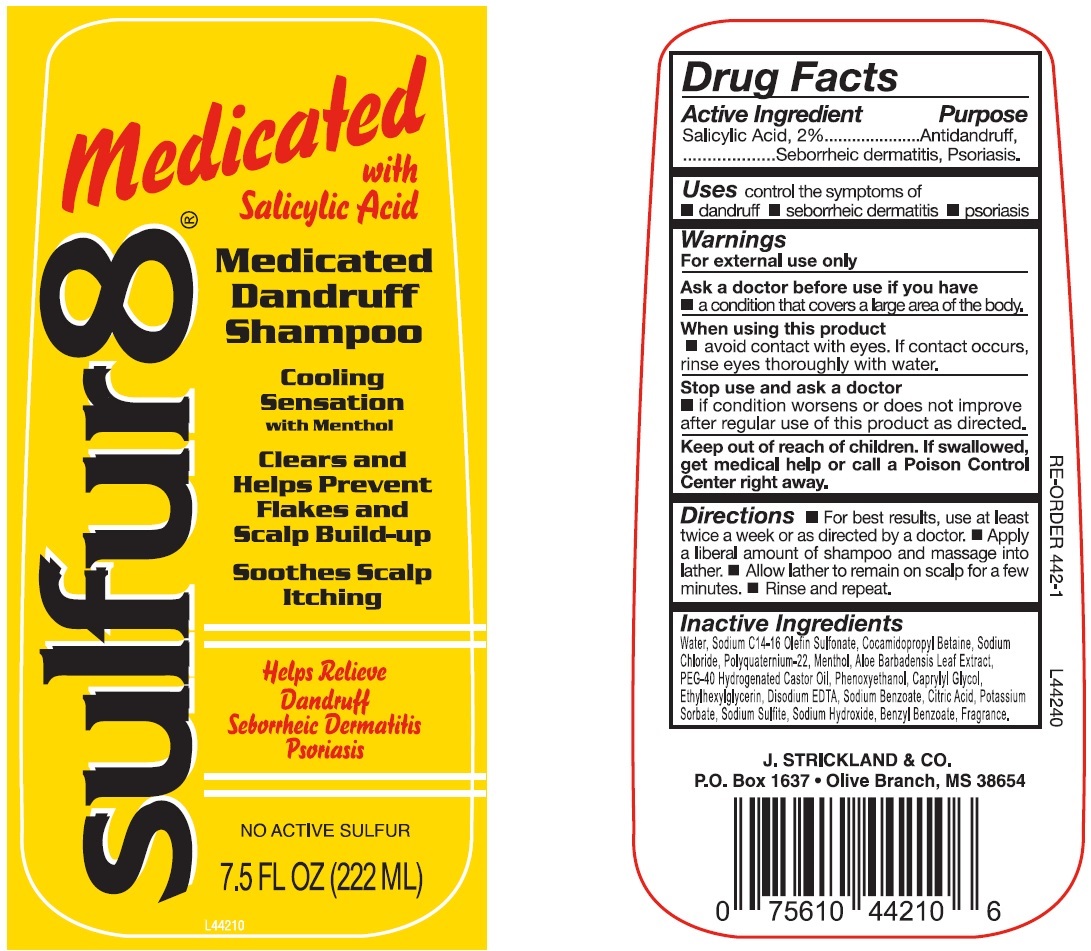 DRUG LABEL: Sulfur 8 Medicated Dandruff with Salicylic Acid
NDC: 12022-039 | Form: LIQUID
Manufacturer: J. Strickland and Co.
Category: otc | Type: HUMAN OTC DRUG LABEL
Date: 20231105

ACTIVE INGREDIENTS: SALICYLIC ACID 20 mg/1 mL
INACTIVE INGREDIENTS: WATER; SODIUM C14-16 OLEFIN SULFONATE; COCAMIDOPROPYL BETAINE; SODIUM CHLORIDE; MENTHOL; ALOE VERA LEAF; POLYOXYL 40 HYDROGENATED CASTOR OIL; PHENOXYETHANOL; CAPRYLYL GLYCOL; ETHYLHEXYLGLYCERIN; EDETATE DISODIUM ANHYDROUS; SODIUM BENZOATE; CITRIC ACID MONOHYDRATE; POTASSIUM SORBATE; SODIUM SULFITE; SODIUM HYDROXIDE; BENZYL BENZOATE

Sulfur 8 Medicated Dandruff Shampoo with Salicylic Acid

Active Ingredient

Salicylic Acid, 2%

Purpose

Antidandruff, Seborrheic dermatitis, Psoriasis.

Uses

control the symptoms of

- dandruff
- seborrheic dermatitis
- psoriasis

Warnings

For external use only

Ask a doctor before use

if you have

- a condition that covers a large area of the body.

When using this product

- avoid contact with eyes. If contact occurs, rinse eyes thoroughly with water.

Stop use and ask a doctor

- if condition worsens or does not improve after regular use of this product as directed.

Keep out of reach of children.

If swallowed, get medical help or call a Poison Control Center right away.

Directions

- For best results, use at least twice a week or as directed by a doctor.
- Apply a liberal amount of shampoo and massage into lather.
- Allow lather to remain on scalp for a few minutes.
- Rinse and repeat.

Inactive Ingrdients

Water, Sodium C14-16 Olefin Sulfonate, Cocamidopropyl Betaine, Sodium Chloride, Polyquaternium-22, Menthol, Aloe Barbadensis Leaf Extract, PEG-40 Hydrogenated Castor Oil, Phenoxyethanol, Caprylyl Glycol, Ethylhexylglycerin, Disodium EDTA, Sodium Benzoate, Citric Acid, Potassium Sorbate, Sodium Sulfite, Sodium Hydroxide, Benzyl Benzoate, Fragrance.